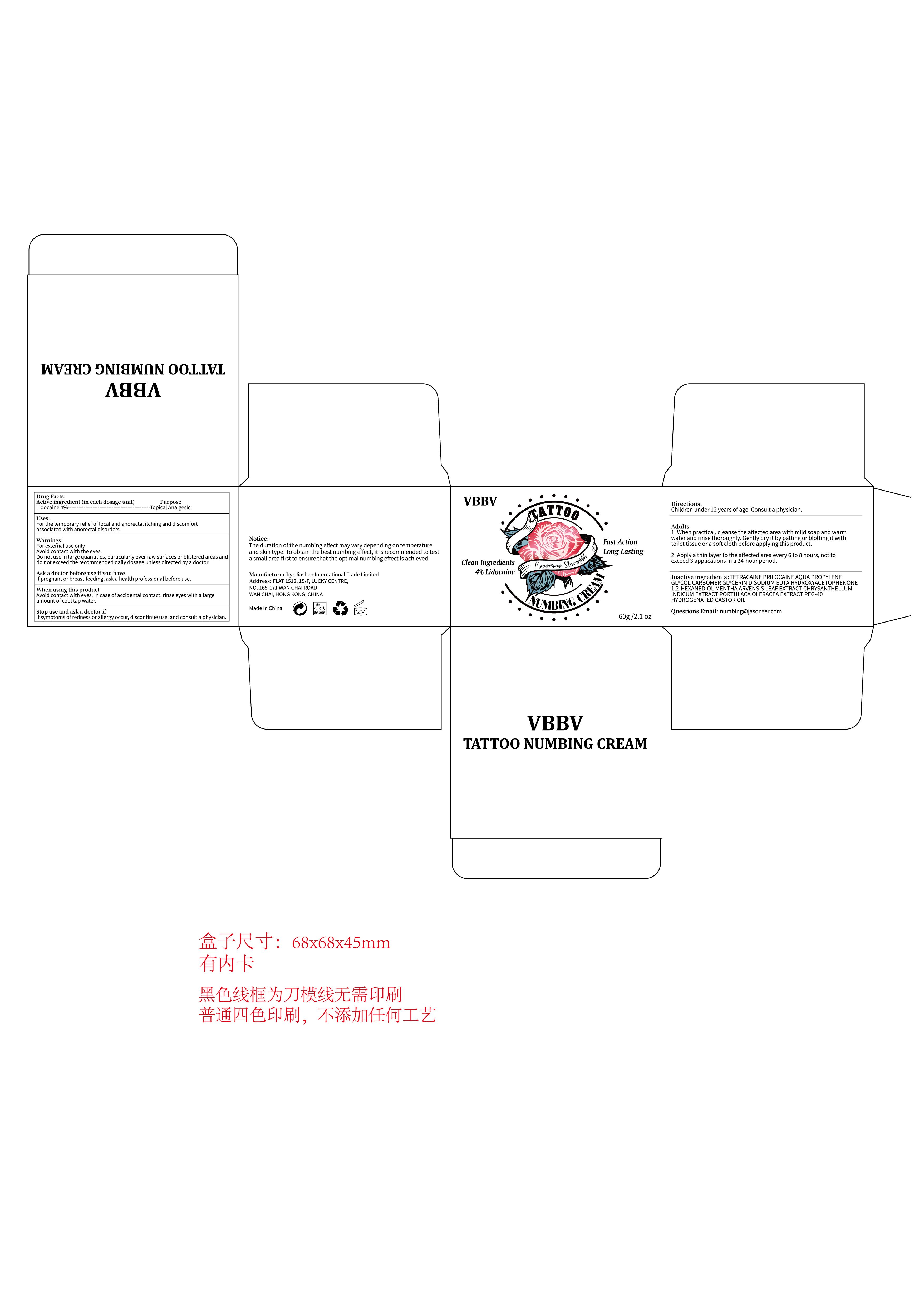 DRUG LABEL: VBBV Tattoo Numbing
NDC: 84867-014 | Form: CREAM
Manufacturer: Jiashen International Trade Limited
Category: otc | Type: HUMAN OTC DRUG LABEL
Date: 20250517

ACTIVE INGREDIENTS: LIDOCAINE 40 mg/1 mL
INACTIVE INGREDIENTS: PROPYLENE GLYCOL; CHRYSANTHELLUM INDICUM TOP; AQUA; MENTHA ARVENSIS LEAF; PURSLANE; 1,2-HEXANEDIOL; TETRACAINE; PEG-40 HYDROGENATED CASTOR OIL; EDETATE DISODIUM; PRILOCAINE; CARBOMER; GLYCERIN; HYDROXYACETOPHENONE

ACTIVE INGREDIENT

Lidocaine 4%

PURPOSE

Uses:For the temporary relief of local and anorectal itching and discomfortassociated with anorectal disorders.

WHEN USING

When using this productAvoid contact with eyes. In case of accidental contact, rinse eyes with a largeamount of cool tap water.

WARNINGS

Warnings:For external use onlyAvoid contact with the eyes.Do not use in large quantities, particularly over raw surfaces or blistered areas anddo not exceed the recommended daily dosage unless directed by a doctor.

Ask a doctor before use if you havelf pregnant or breast-feeding, ask a health professional before use.

Stop use and ask a doctor if
lf symptoms of redness or allergy occur, discontinue use, and consult a physician.

Directions:
Children under 12 years of age: Consult a physician.

DOSAGE AND ADMINISTRATION

Adults:1. When practical, cleanse the affected area with mild soap and warmwater and rinse thoroughly. Gently dry it by patting or blotting it withtoilet tissue or a soft cloth before applying this product.
2. Apply a thin layer to the affected area every 6 to 8 hours, not toexceed 3 applications in a 24-hour period.

INACTIVE INGREDIENT

Inactive ingredientS:TETRACAINE PRILOCAINE AQUA PROPYLENEGLYCOL CARBOMER GLYCERIN DISODIUM EDTA HYDROXYACETOPHENONE1,2-HEXANEDIOL MENTHA ARVENSIS LEAF EXTRACT CHRYSANTHELLUMINDICUM EXTRACT PORTULACA OLERACEA EXTRACT PEG-40HYDROGENATED CASTOR OIL

KEEP OUT OF REACH OF CHILDREN

Children under 12 years of age: Consult a physician. keep out of reach of children